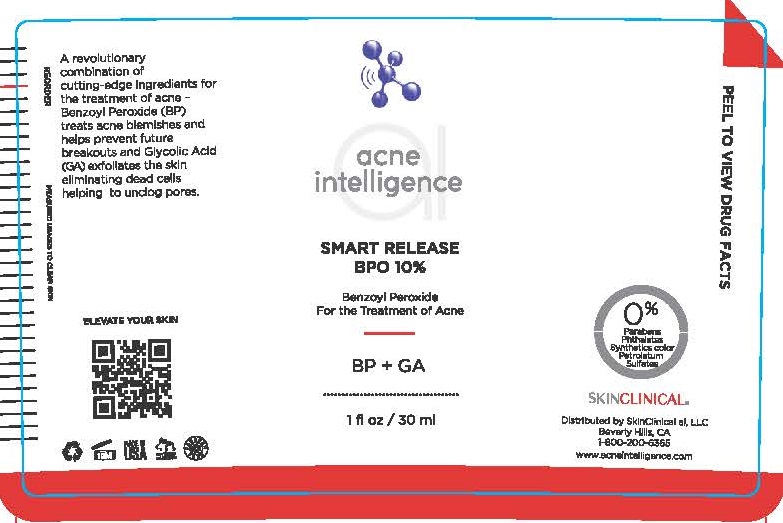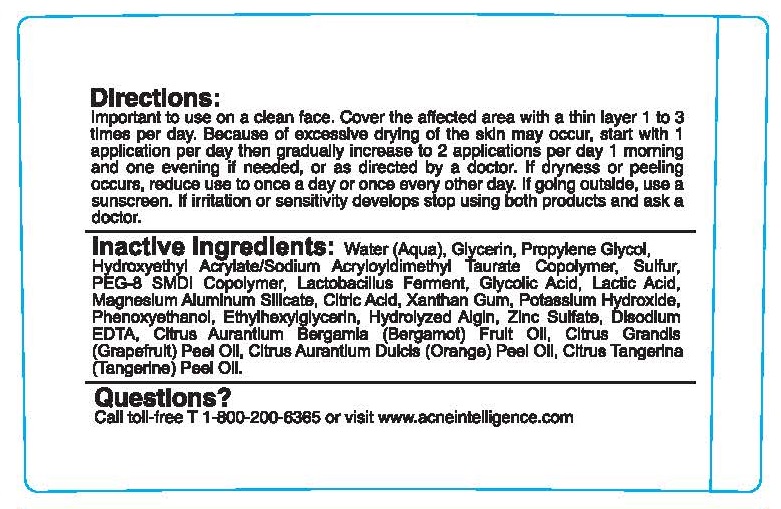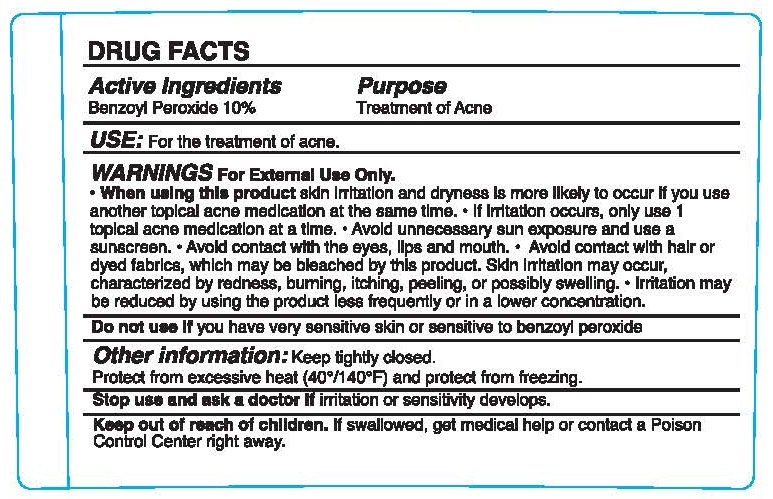 DRUG LABEL: SMART RELEASE BPO
NDC: 73110-105 | Form: LOTION
Manufacturer: SkinClinical AI, LLC
Category: otc | Type: HUMAN OTC DRUG LABEL
Date: 20190906

ACTIVE INGREDIENTS: BENZOYL PEROXIDE 10 g/100 mL
INACTIVE INGREDIENTS: WATER; GLYCERIN; PROPYLENE GLYCOL; HYDROXYETHYL ACRYLATE/SODIUM ACRYLOYLDIMETHYL TAURATE COPOLYMER (100000 MPA.S AT 1.5%); PEG-8/SMDI COPOLYMER; LACTOBACILLUS REUTERI; GLYCOLIC ACID; LACTIC ACID; MAGNESIUM ALUMINUM SILICATE; ANHYDROUS CITRIC ACID; XANTHAN GUM; POTASSIUM HYDROXIDE; PHENOXYETHANOL; ETHYLHEXYLGLYCERIN; SODIUM ALGINATE; ZINC SULFATE; EDETATE DISODIUM; BERGAMOT OIL; GRAPEFRUIT OIL; ORANGE OIL; TANGERINE PEEL; SULFUR

SMART RELEASE BPO 10%

Active ingredients

BENZOYL PEROXIDE 10%

PURPOSE

TREATMENT OF ACNE

USE

For the treatment of acne.

WARNINGS

For External Use Only.

When using this product skin irritation and dryness is more likely to occur if you use another topical acne medication at the same time.

- If irritation occurs, only use 1 topical acne medication at a time.
- Avoid unnecessary sun exposure and use a sunscreen.
- Avoid contact with the eyes, lips and mouth.
- Avoid contact with hair or dyed fabrics, which may be bleached by this product. Skin irritation may occur, characterized by redness, burning, itching, peeling, or possibly swelling.
- Irritation may be reduced by usi ng the product less frequently or in a lower concentration.

Do not use if you have very sensitive skin or sensitive to benzoyl peroxide.

Other information

Keep tightly closed.
Protect from excessive heat (40° / 140° F) and protect from freezing

Stop use and ask a doctor if irritation or sensitivity develops.

Keep out of reach of children. If swallowed, get medical help or contact a Poison Control Center right away.

DIRECTIONS

Important to use on a clean face. Cover the affected area with a thin layer 1 to 3 times per day. Because of excessive drying of the skin may occur, start with 1 application per day then gradually increase to 2 applications per day 1 morning and one evening if needed, or as directed by a doctor. If dryness or peeling occurs, reduce use to once a day or once every other day. If going outside, use a sunscreen. If irritation or sensitivity develops stop using both products and ask a doctor.

INACTIVE INGREDIENTS

Water (Aqua), Glycerin, Propylene Glycol, Hydroxyethyl Acrylate/Sodium Acryloyldimethyl Taurate Copolymer, Sulfur, PEG-8 SMDI Copolymer, Lactobacillus Ferment, Glycolic Acid, Lactic Acid, Magnesium Aluminum SIlicate, Citric Acid, Xanthan Gum, Potassium Hydroxide, Phenoxyethanol, Ethylhexylglycerin, Hydrolyzed Algin, Zinc Sulfate, Disodium EDTA, Citrus Aurantium Bergamia (Bergamo!} Fruit Oil, Citrus Grandis (Grapefruit) Peel Oil, Citrus Aurantium Dulcis (Orange) Peel Oil, Citrus Tangerina (Tangerine) Peel Oil

QUESTIONS?

CALL TOLL-FREE T 1-800-200-6365 OR VISIT WWW.ACNEINTELLIGENCE.COM